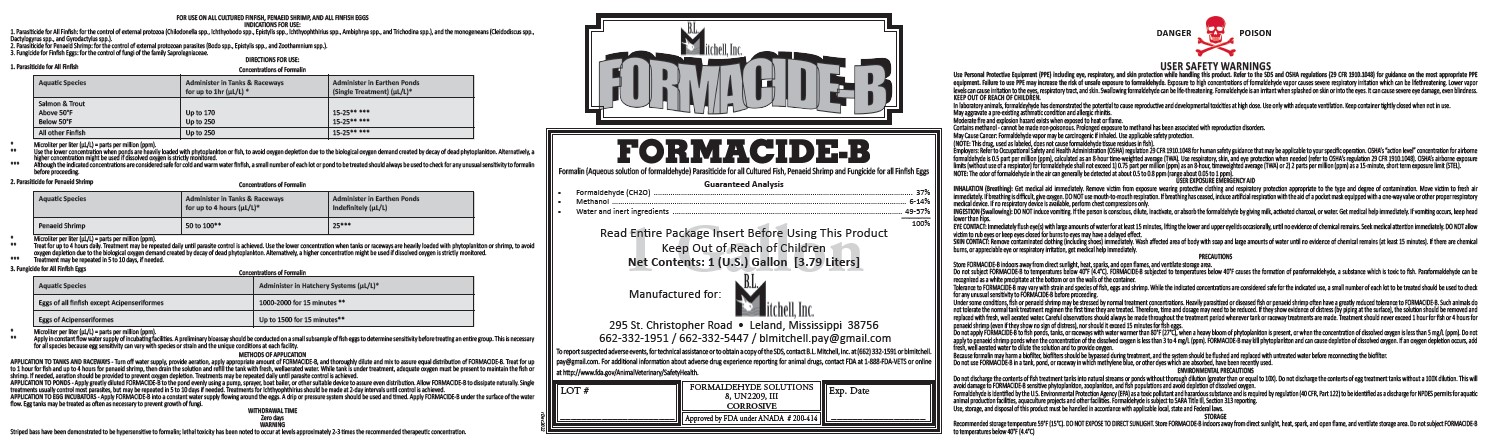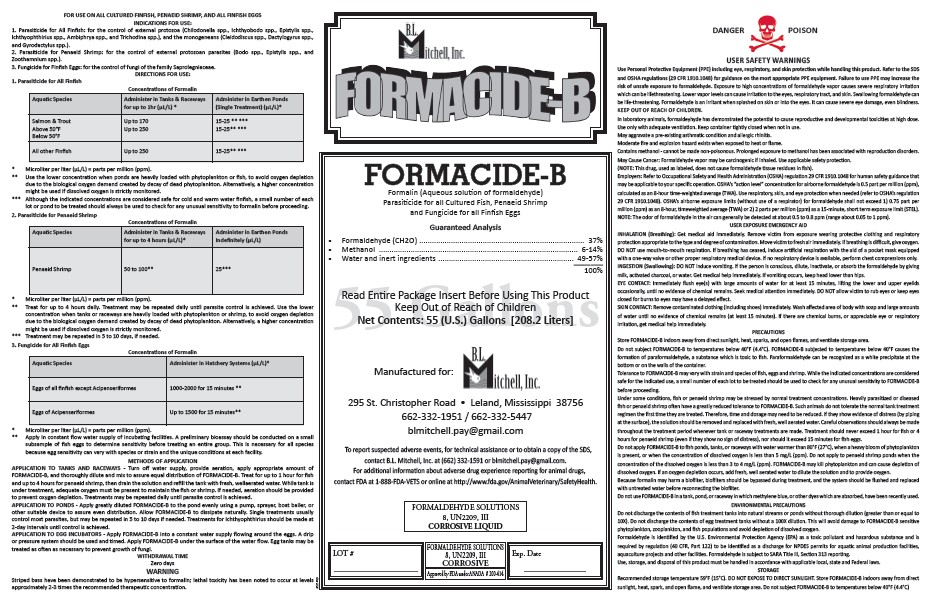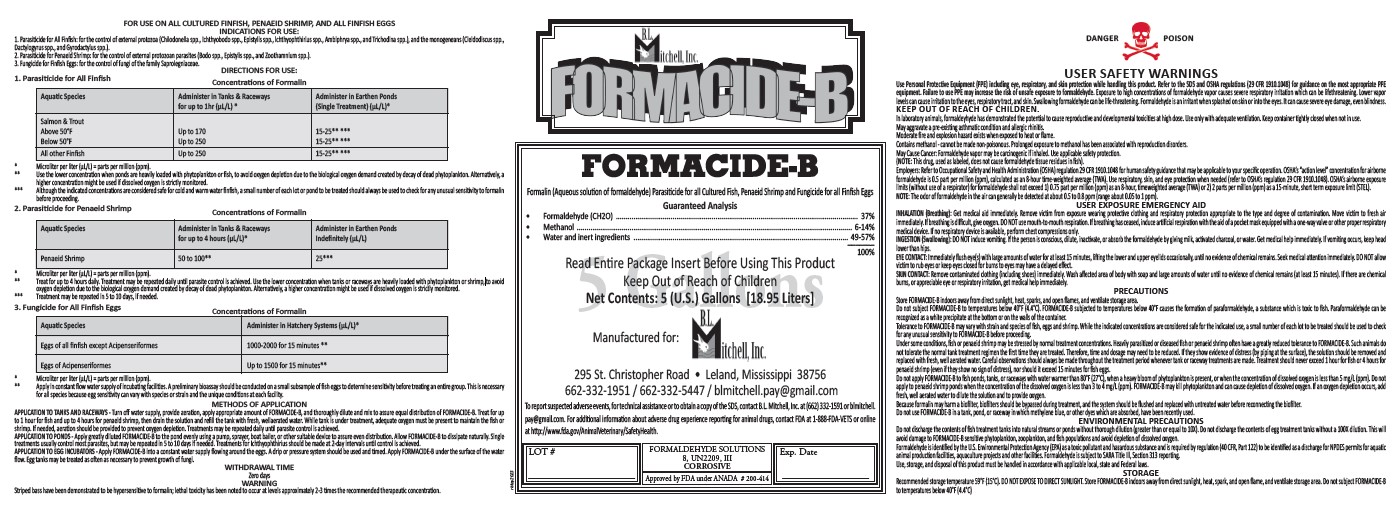 DRUG LABEL: FORMACIDE-B
NDC: 67188-101 | Form: LIQUID
Manufacturer: B. L. Mitchell, Inc.
Category: animal | Type: OTC ANIMAL DRUG LABEL
Date: 20230714

ACTIVE INGREDIENTS: FORMALDEHYDE 0.037 kg/1 L; METHYL ALCOHOL 0.014 kg/1 L
INACTIVE INGREDIENTS: WATER

BL MITCHELL (as PLD) - FORMACIDE-B (67188-101)

ACTIVE INGREDIENT

FORMALDEHYDE (CH2O)....37%

METHANOL.....6-14%

WATER AND INERT INGREDIENTS... 49-57%

PURPOSE

FORMACIDE-B

FORMALIN (AQUEOUS SOLUTION OF FORMALDEHYDE)

PARASITIDE FOR ALL CULTURED FISH